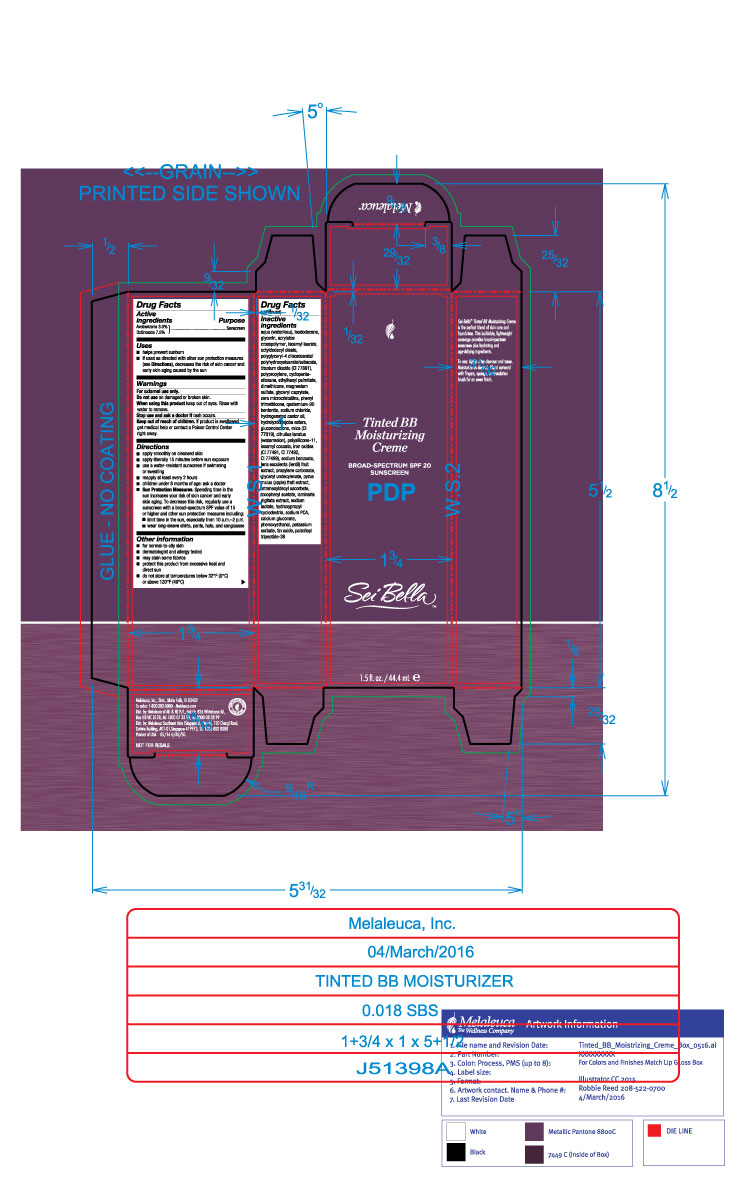 DRUG LABEL: Sei Bella Tinted BB Moisturizing Creme Broadspectrum SPF 20
NDC: 54473-263 | Form: LOTION
Manufacturer: Melaleuca Inc
Category: otc | Type: HUMAN OTC DRUG LABEL
Date: 20160506

ACTIVE INGREDIENTS: AVOBENZONE 1.389 g/44.4 mL; OCTINOXATE 3.473 g/44.4 mL
INACTIVE INGREDIENTS: LENTIL; PROPYLENE CARBONATE; TETRAHEXYLDECYL ASCORBATE; ALPHA-TOCOPHEROL ACETATE; SODIUM LACTATE; WATER; ISODODECANE; 1,1'-((1-METHYL-1,2-ETHANEDIYL)2-PROPENOIC ACID, BIS(OXY(1-METHYL-2,1-ETHANEDIYL))) ESTER; ISOAMYL LAURATE; ETHYLHEXYL PALMITATE; MAGNESIUM SULFATE; MICROCRYSTALLINE WAX; PHENYL TRIMETHICONE; HYDROGENATED CASTOR OIL; STANNIC OXIDE; CITRULLUS LANATUS VAR. LANATUS WHOLE; GLYCERYL MONOUNDECYLENATE; GLYCERIN; OCTYLDODECYL OLEATE; ISOLAN; CYCLOMETHICONE; ISOAMYL COCOATE; SODIUM BENZOATE; GLUCONOLACTONE; PHENOXYETHANOL; MICA; APPLE FRUIT OIL; LAMINARIA DIGITATA; DIMETHICONE; GLYCERYL CAPRYLATE; SODIUM CHLORIDE; HYDROLYZED JOJOBA ESTERS (ACID FORM); CALCIUM GLUCONATE; POTASSIUM SORBATE; TITANIUM DIOXIDE

Tinted BB Moisturizing Creme Broad-Spectrum SPF 20 Sunscreen

Active Ingredients

Avobenzone 3.0%

Octinoxate 7.5%

Purpose

Sunscreen

Uses

- helps prevent sunburn
- is used as directed with other sun protection measures (see Directions), decreases the risk of skin cancer and early skin aging caused by the sun

Warnings

For External Use Only

Keep out of the reach of children. If swallowed, get medical help or contact a Poison Control Center right away.

When using

When using this product keep out of eyes. Rinse with water to remove.

Do not use on damaged or broken skin.

Directions

- apply smoothly on cleased skin
- apply liberally 15 minutes before sun exposure
- use a water-resistant sunscreen if swimming or sweating
- reapply at least every 2 hours
- children under 6 months of age: ask a doctor
- Sun Protection Measures: Spending time in the sun increases your risk of skin cancer and early skin aging. To decrease this risk, regularly use a sunscreen with a broad-spectrum SPF value of 15 or higher and other sun protection measures including:
- limit time in the sun, especially from 10a.m.-2p.m
- wear long-sleeve shirts, pants, hats, and sunglasses

Other Information

- may stain some fabrics
- protect this product from excessive heat and direct sun
- do not store at temperatures below 32oF (0oC) or above 120oF (49oC)

Other Information

dermatologist and allergy tested

Inactive ingredients

aqua (water/eau), isododecane, glycerin, acrylates crosspolymer, isoamyl laurate, octyldodecyl oleate, polyglyceryl-4 diisostearate/polyhydroxustearate/sebacate, titanium dioxide (CI 77891), polypropylene, cyclopentasiloxane, ethylhexyl palmitate, dimethicone, magnesium sulfate, glyceryl caprylate, microcrystalline wax, phenyl trimethicone, quaternium-90 bentonite, sodium chloride, hydrogenated castor oil, hydrolyzed jojoba esters, gluconolactone, mica (CI 77019), citrullur lanatus (watermelon), polysilicone-11, isoamyl cocoate, iron oxides (CI 77491, CI 77492, CI 77499), sodium benzoate, lens esculenta (lentil) fruit extract, propylene carbonate, glyceryl undecylenate, pyrus malus (apple) fruit extract, tetrahexyldecyl ascorbate, tocopheryl acetate, laminaria digitata extract, sodium lactate, hydroxypropyl cyclodextrin, sodium PCA, calcium gluconate, phenoxyethanol, potassium sorbate, tin oxide, palmitoyl tripeptide-38